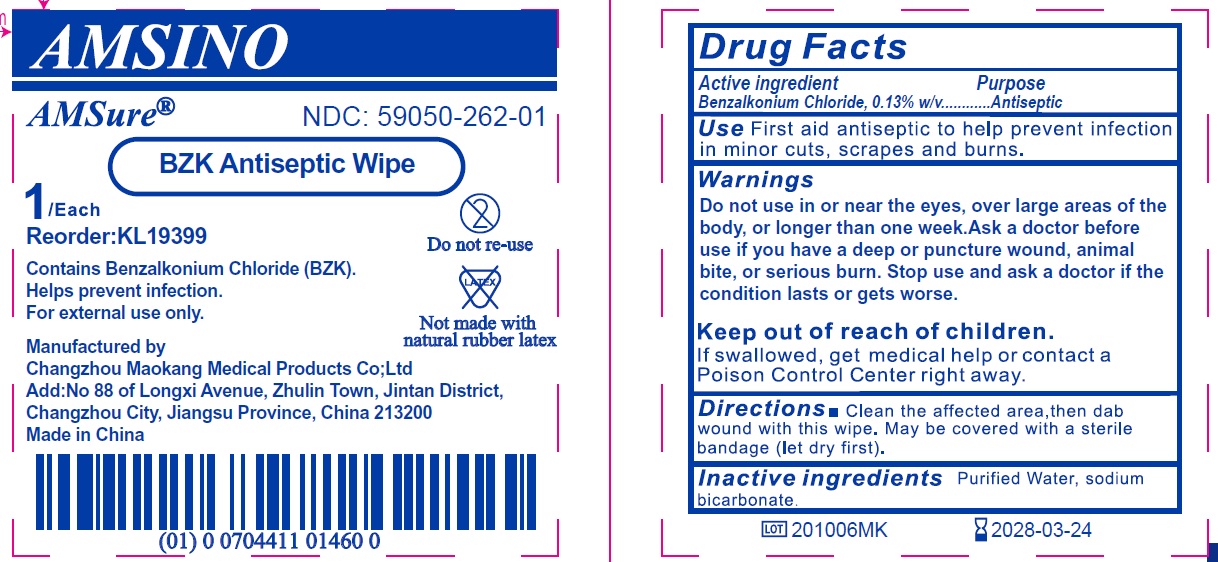 DRUG LABEL: BZK Antiseptic Wipe
NDC: 59050-262 | Form: CLOTH
Manufacturer: Changzhou Maokang Medical Products Co., Ltd
Category: otc | Type: HUMAN OTC DRUG LABEL
Date: 20241121

ACTIVE INGREDIENTS: BENZALKONIUM CHLORIDE 1.3 mg/1 g
INACTIVE INGREDIENTS: WATER; SODIUM BICARBONATE

BZK Antiseptic Wipe

Active ingredient

Benzalkonium Chloride, 0.13% w/v

Purpose

Antiseptic

Use

First aid antiseptic to help prevent infection in minor cuts, scrapes and burns.

Warnings

Do not use

in or near the eyes, over large areas of the body, or longer than one week.

Ask a doctor before use if

you have a deep or puncture wound, animal bite, or serious burn.

Stop use and ask a doctor if

the condition lasts or gets worse.

Keep out of reach of children.

If swallowed, get medical help or contact a Poison Control Center right away.

Directions

- Clean the affected area. then dab wound with this wipe. May be covered with a sterile bandage (let dry first).

Inactive ingredients

Purified Water, sodium bicarbonate.